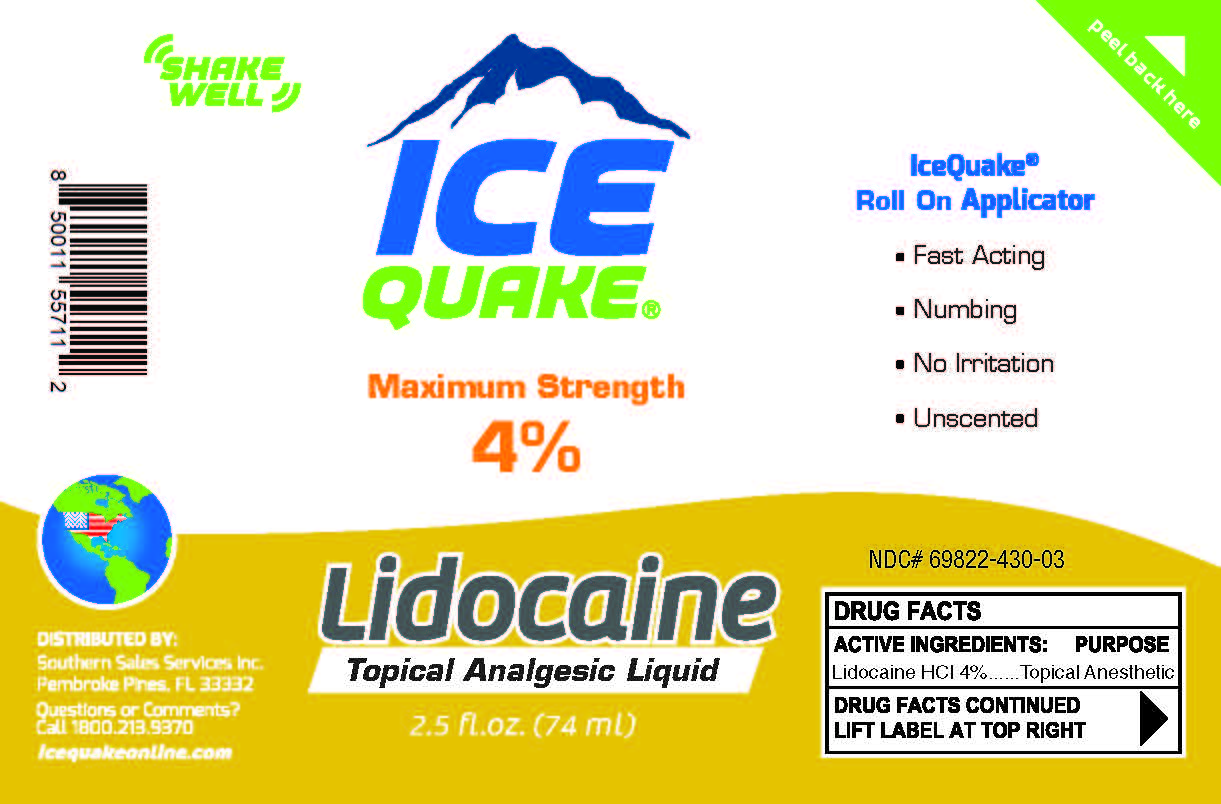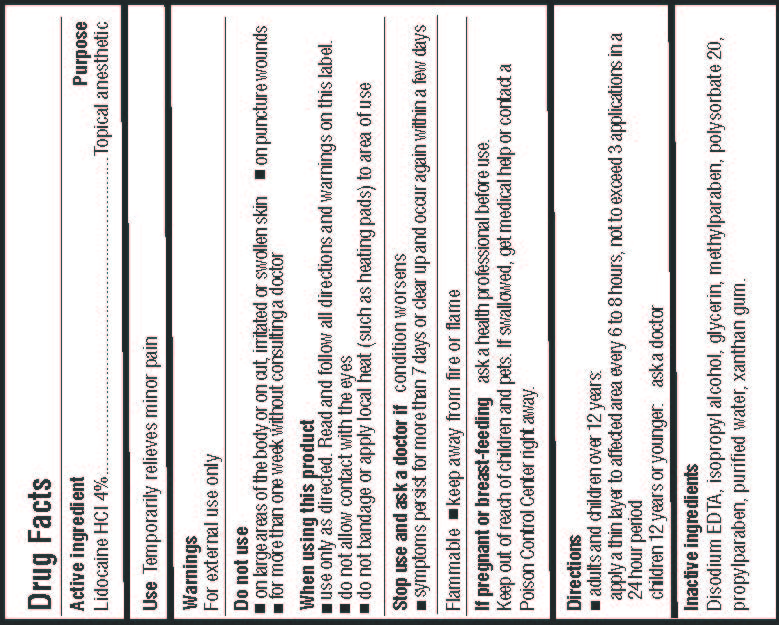 DRUG LABEL: IceQuake Lidocaine Analgesic
NDC: 69822-430 | Form: LIQUID
Manufacturer: Southern Sales & Service, Inc.
Category: otc | Type: HUMAN OTC DRUG LABEL
Date: 20231129

ACTIVE INGREDIENTS: LIDOCAINE HYDROCHLORIDE 4 g/100 mL
INACTIVE INGREDIENTS: EDETATE DISODIUM ANHYDROUS; ISOPROPYL ALCOHOL; GLYCERIN; METHYLPARABEN; POLYSORBATE 20; PROPYLPARABEN; WATER; XANTHAN GUM

IceQuake Lidocaine Analgesic

Active ingredient

Lidocine HCl 4%

Purpose

Topical anesthetic

Use

Temporarily relieves minor pain

Warnings

For external use only

Do not use

- on large areas of the body or on cut, irritated or swollen skin
- on puncture wounds
- for more than one week without consulting a doctor

When using this product

- use only as directed. Read and follow all directions and warnings on this label.
- do not allow contact with the eyes
- do not bandage or apply local heat (such as heating pads) to area of use

Do not use

- on large areas of the body or on cut, irritatred or swollen skin
- on puncture wounds
- for more than one week without consulting a doctor

condition worsens Stop use and ask a doctor if

- symptoms persist for more than 7 days or clear up and occur again within a few days

Flammable

keep away from fire or flame

If pregnant or breast-feeding

ask a health professional before use.

Keep out of reach of children

and pets. If swallowed, get medical help or contact a Poison Control Center right away.

Directions

- adults and children over 12 years:

apply a thin layer to affected area every 6 to 8 hours, not to exceed 3 applications in a 24 hour period

children 12 years or younger: ask a doctor

Inactive ingredients

Disodium EDTA, isopropyl alcohol, glycerin, methylparaben, polysorbate 20, propylparaben, purified water, xanthan gum.